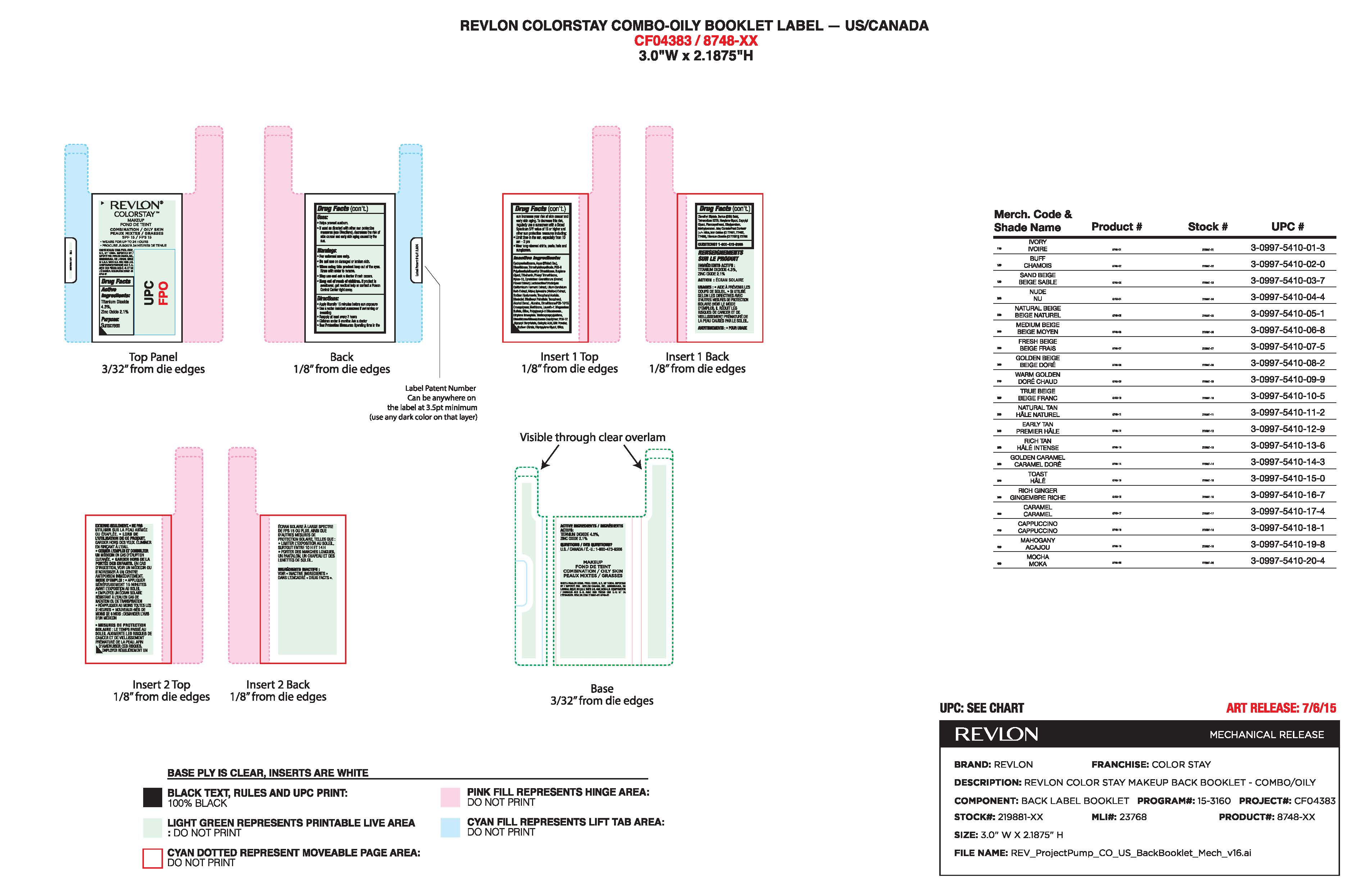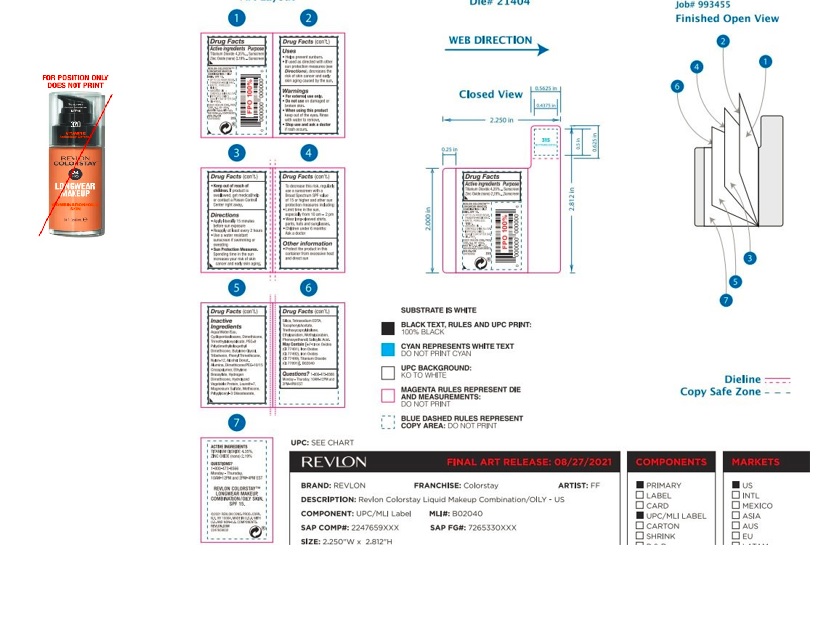 DRUG LABEL: Revlon Colorstay Liquid Makeup for Oily to Combination Skin
NDC: 10967-642 | Form: LIQUID
Manufacturer: Revlon Consumer Products Corp
Category: otc | Type: HUMAN OTC DRUG LABEL
Date: 20241231

ACTIVE INGREDIENTS: ZINC OXIDE 2.1 mg/1 mL; TITANIUM DIOXIDE 4.3 mg/1 mL
INACTIVE INGREDIENTS: WATER; DIMETHICONE; BUTYLENE GLYCOL; PHENYL TRIMETHICONE; METHICONE (20 CST); LAURETH-7; PHENOXYETHANOL; METHYLPARABEN; ETHYLPARABEN; CYCLOMETHICONE 5; TRIMETHYLSILOXYSILICATE (M/Q 0.6-0.8); PEG-9 POLYDIMETHYLSILOXYETHYL DIMETHICONE; TRIBEHENIN; NYLON-12; ALCOHOL; ALUMINUM OXIDE; MAGNESIUM SULFATE, UNSPECIFIED FORM; SILICON DIOXIDE; HYALURONATE SODIUM; POLYGLYCERYL-3 DIISOSTEARATE; ETHYLENE BRASSYLATE; TRIETHOXYCAPRYLYLSILANE; .ALPHA.-TOCOPHEROL ACETATE; EDETATE SODIUM; SODIUM CITRATE; LEVOMENOL; ETHYLHEXYL PALMITATE; TOCOPHEROL; DIPROPYLENE GLYCOL; SALICYLIC ACID; MALVA SYLVESTRIS FLOWERING TOP; LILIUM CANDIDUM BULB; CYMBIDIUM HOOKERIANUM FLOWER; HEXYLENE GLYCOL; CAPRYLYL GLYCOL

Revlon Colorstay Liquid Makeup for Oily to Combination Skin

Active Ingredients:

Titanium Dioxide 4.35 %

Zinc Oxide (nano) 2.19 %

Purpose:

Sunscreen

Uses:

- Helps prevent sunburn
- If used as directed with other sun protection measures (see Directions), decreases the risk of skin cancer and early skin aging caused by the sun

Warnings:

- For external use only
- Do notuse on damaged or broken skin
- When using this product: Keep out of eyes. Rinse with water to remove.
- Stop use and ask a doctor if a rash occurs
- Keep out of reach of children. If product is swallowed, get medical help or contact a Poison Control center right away

Directions:

- Apply liberally 15 minutes before sun exposure
- Use a water resistant sunscreen if swimming or sweating
- Reapply at least every 2 hours
- Children under 6 months: Ask a doctor.

Sun Protection Measures:

Spending time in the sun increases your risk of skin cancer and early skin aging. To decrease this risk, regularly use a sunscreen with a Broad Spectrum SPF value of 15 or higher and other sun protection measures including:

- Limit time in the sun, especially from 10 am - 2 pm
- Wear long-sleeved shirts, pants, hats and sunglasses.

Inactive Ingredients:

Aqua/Water/Eau, Cyclopentasiloxane, Dimethicone, Trimethylsiloxysilicate, PEG-9 Polydimethylsiloxyethyl Dimethicone, Butylene Glycol, Tribehenin, Phenyl Trimethicone, Nylon-12, Alcohol Denat., Alumina, Dimethicone/PEG-10/15 Crosspolymer, Ethylene Brassylate, Hydrogen Dimethicone, Hydrolyzed Vegetable Protein, Laureth-7, Magnesium Sulfate, Methicone, Polyglyceryl-3 Diisostearate, Silica, Tetrasodium EDTA, Tocopheryl Acetate, Triethoxycaprylylsilane, Ethylparaben, Methylparaben, Phenoxyethanol, Salicylic Acid.

MAY CONTAIN:

Iron Oxides (CI 77491) Iron Oxides (CI 77492) Iron Oxides (CI 77499) Titanium Dioxide (CI 77891

PURPOSE

Sunscreen

KEEP OUT OF REACH OF CHILDREN

Keep out of the reach of children. If product is swallowed, get medical help or contact a Poison Control Center right away.

DOSAGE AND ADMINISTRATION

Apply liberally 15 minutes before sun exposure.

Principal Display Panel:

REVLON

Colorstay Makeup

Combination/Oily Skin

SPF 15